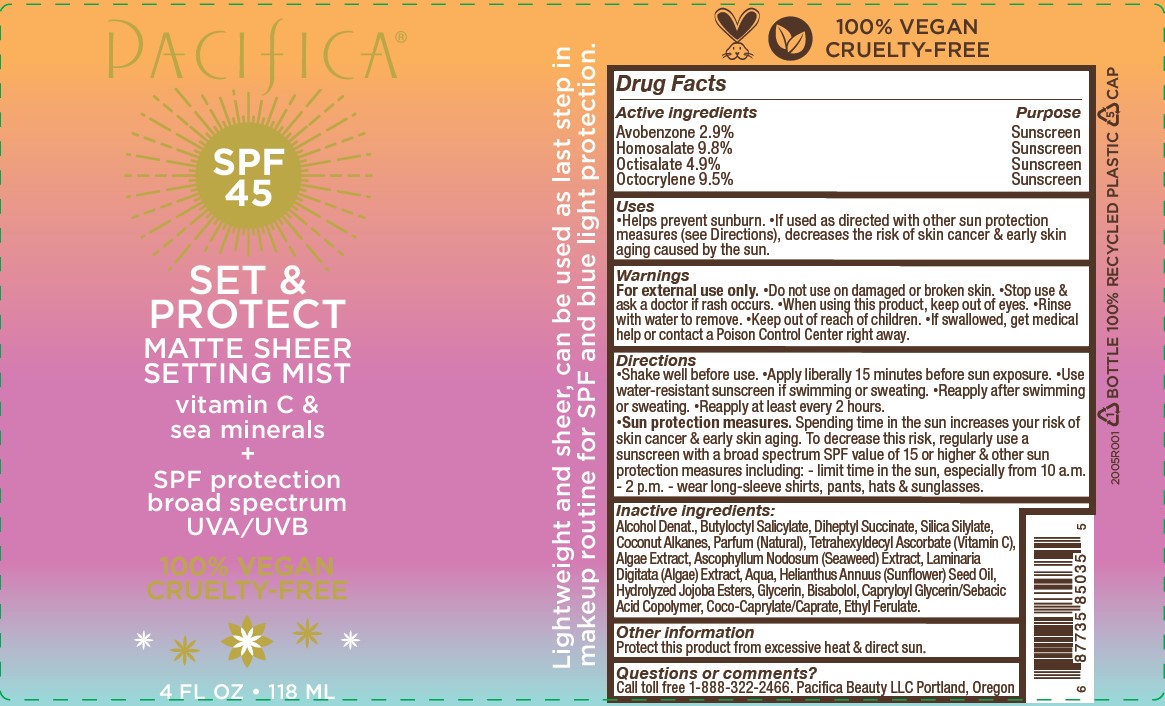 DRUG LABEL: Glow Baby Brightening Setting Mist SPF 45
NDC: 61197-205 | Form: SPRAY
Manufacturer: Pacifica Beauty, LLC
Category: otc | Type: HUMAN OTC DRUG LABEL
Date: 20250103

ACTIVE INGREDIENTS: HOMOSALATE 9.8 mg/100 mL; OCTISALATE 4.9 mg/100 mL; AVOBENZONE 2.9 mg/100 mL; OCTOCRYLENE 9.5 mg/100 mL
INACTIVE INGREDIENTS: ALCOHOL; SILICA DIMETHYL SILYLATE; TETRAHEXYLDECYL ASCORBATE; FUCUS SERRATUS; ASCOPHYLLUM NODOSUM; DIHEPTYL SUCCINATE; ETHYL FERULATE; LAMINARIA DIGITATA; GLYCERIN; CAPRYLOYL GLYCERIN/SEBACIC ACID COPOLYMER (2000 MPA.S); SUNFLOWER OIL; HYDROLYZED JOJOBA ESTERS (ACID FORM); BUTYLOCTYL SALICYLATE; COCONUT ALKANES; .ALPHA.-BISABOLOL, (+)-; COCO-CAPRYLATE/CAPRATE; WATER

Glow Baby Brightening Setting Mist SPF 45

Active ingredients Purpose

Avobenzone 2.9 % Sunscreen

Homosalate 9.8% Sunscreen

Octisalate 4.9% Sunscreen

Octocrylene 9.5% Sunscreen

Uses

Helps prevent sunburn. If used as directed with other sun protection measures (see Directions), decreases the risk of skin cancer & early skin aging caused by the sun.

INDICATIONS AND USAGE

If used as directed with other sun protection measures (see Directions), decreases the risk of skin cancer & early skin aging caused by the sun.

Warnings

For external use only. Do not use on damaged or broken skin. Stop use & ask a doctor if rash occurs. When using this product, keep out of eyes. Rinse with water to remove. Keep out of reach of children. If swallowed, get medical help or contact a Poison Control Center right away.

Keep out of reach of children.

Directions

Shake well before use. Apply liberally 15 minutes before sun exposure. Use water-resistant sunscreen if swimming or sweating. Reapply after swimming or sweating. Reapply at least every 2 hours.

Sun protection measures. Spending time in the sun increases your risk of skin cancer & early skin aging. To decrease this risk, regularly use a sunscreen with a broad spectrum SPF value of 15 or higher & other sun protection measures including: - limit time in the sun, especially from 10 a.m. - 2 p.m. - wear long-sleeve shirts, pants, hats & sunglasses.

Inactive ingredients:

Alcohol Denat., Butyloctyl Salicylate, Diheptyl Succinate, Silica Silylate, Coconut Alkanes, Parfum (Natural), Tetrahexyldecyl Ascorbate (Vitamin C), Algae Extract, Ascophyllum Nodosum (Seaweed) Extract, Laminaria Digitata (Algae) Extract, Aqua, Helianthus Annuus (Sunflower) Seed Oil, Hydrolyzed Jojoba Esters, Glycerin, Bisabolol, Capryloyl Glycerin/Sebacic Acid Copolymer, Coco Caprylate/Caprate, Ethyl Ferulate.

Other information

Protect this product from excessive heat & direct sun.

Questions or comments?

Call toll free 1-888-322-2466. Pacifica Beauty LLC Portland, Oregon